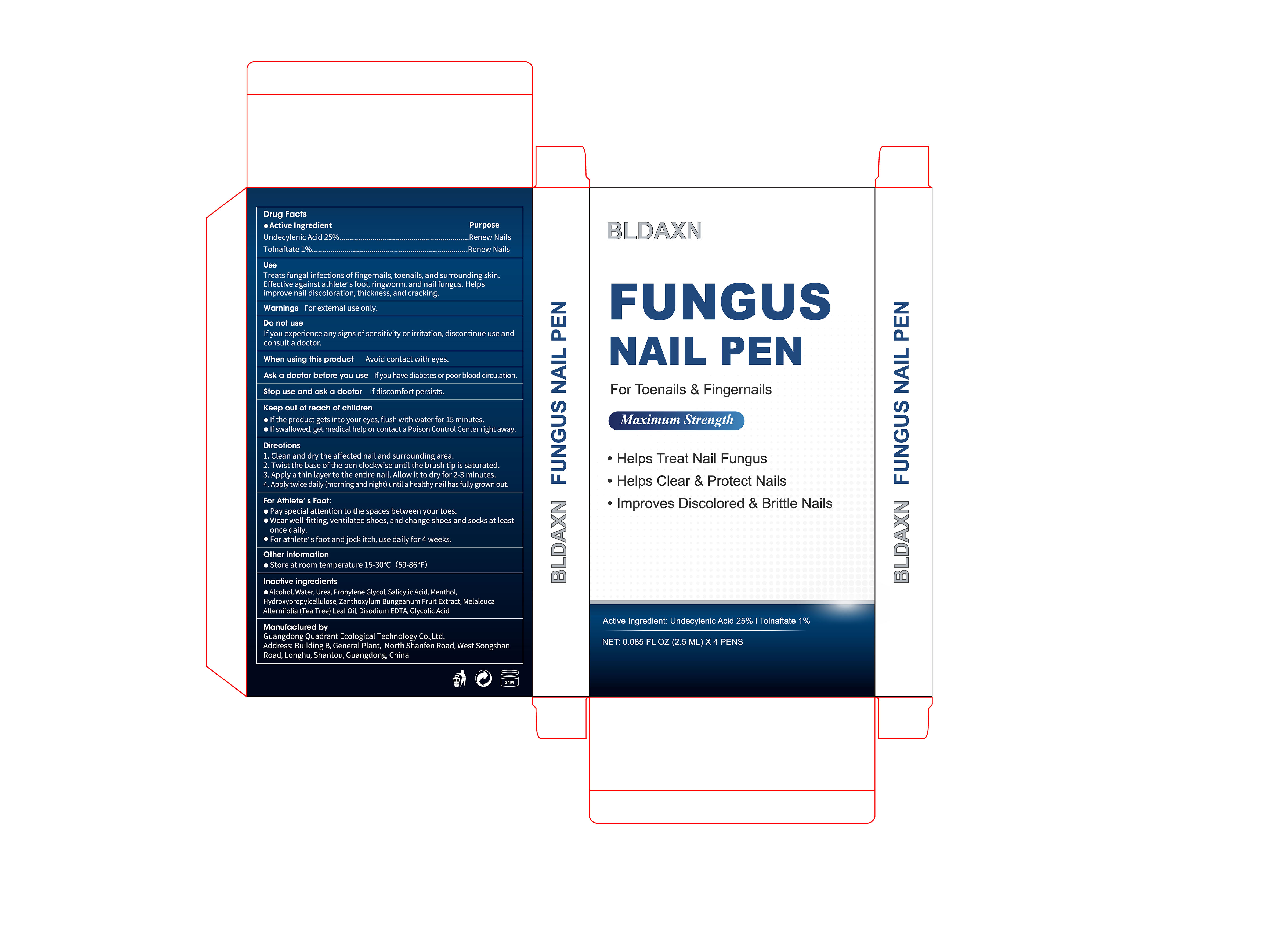 DRUG LABEL: BLDAXN FUNGUS NAIL PEN
NDC: 76986-026 | Form: LIQUID
Manufacturer: Guangdong Quadrant Ecological Technology Co., Ltd.
Category: otc | Type: HUMAN OTC DRUG LABEL
Date: 20260202

ACTIVE INGREDIENTS: TOLNAFTATE 0.01 g/1 mL; UNDECYLENIC ACID 0.25 g/1 mL
INACTIVE INGREDIENTS: SALICYLIC ACID; HYDROXYPROPYLCELLULOSE; MENTHOL; ALCOHOL; WATER; MELALEUCA ALTERNIFOLIA (TEA TREE) LEAF OIL; UREA; ZANTHOXYLUM BUNGEANUM FRUIT; PROPYLENE GLYCOL; EDETATE DISODIUM; GLYCOLIC ACID

76986-026 BLDAXN FUNGUS NAIL PEN

ACTIVE INGREDIENT

UNDECYLENIC ACID 25%
TOLNAFTATE 1%

PURPOSE

Renew Nails

INDICATIONS AND USAGE

Treats fungal infections of fingernails, toenails, and surrounding skin.Effective against athlete's foot, ringworm, and nail fungus. Helps improve nail discoloration, thickness, and cracking.

WARNINGS

For external use only.

DO NOT USE

If you experience any signs of sensitivity or irritation, discontinue use and consult a doctor.

When using this product Avoid contact with eyes.

Stop use and ask a doctor If discomfort persists.

KEEP OUT OF REACH OF CHILDREN

If the product gets into your eyes, flush with water for 15 minutes.
Ifswallowed, get medical help or contact a Poison Control Center right away.

DOSAGE AND ADMINISTRATION

1. Clean and dry the affected nail and surrounding area.

2. Twist the base of the pen clockwise until the brush tip is saturated

3. Apply a thin layer to the entire nail. Allow it to dry for 2-3 minutes.

4. Apply twice daily (morning and night) until a healthy nail has fully grown out.

INACTIVE INGREDIENT

ALCOHOL
WATER
UREA
PROPYLENE GLYCOL
SALICYLIC ACID
MENTHOL
HYDROXYPROPYLCELLULOSE
ZANTHOXYLUM BUNGEANUM FRUIT EXTRACT
MELALEUCA ALTERNIFOLIA (TEA TREE) LEAF OIL
DISODIUM EDTA
GLYCOLIC ACID